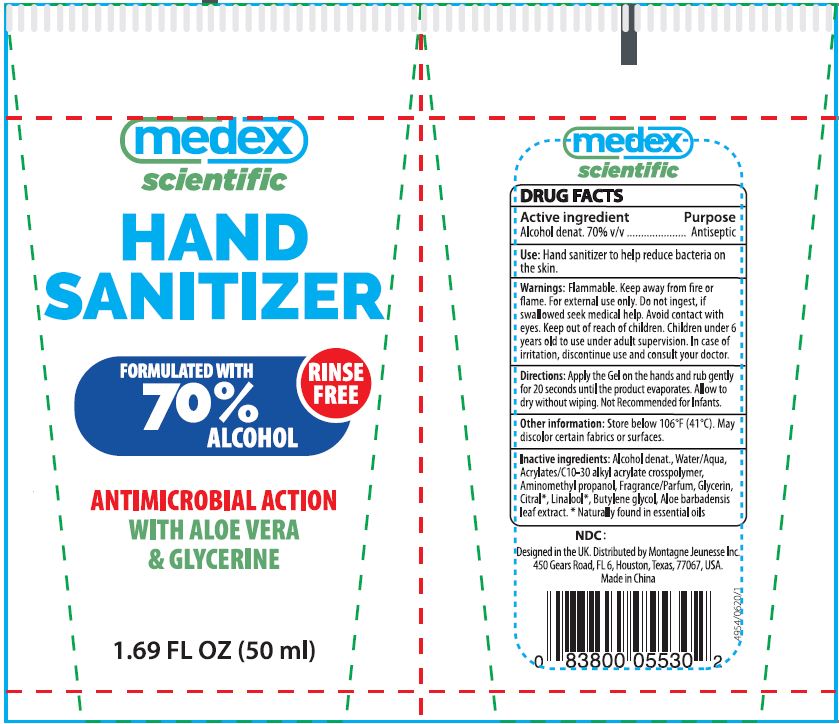 DRUG LABEL: HAND SANITIZER
NDC: 76854-102 | Form: GEL
Manufacturer: Fujian Shuangfei Daily Chemicals Co.,Ltd.
Category: otc | Type: HUMAN OTC DRUG LABEL
Date: 20200623

ACTIVE INGREDIENTS: ALCOHOL 70 mL/100 mL
INACTIVE INGREDIENTS: WATER; CARBOMER INTERPOLYMER TYPE A (ALLYL SUCROSE CROSSLINKED); AMINOMETHYLPROPANOL; GLYCERIN; CITRAL; LINALOOL, (+)-; BUTYLENE GLYCOL; ALOE VERA LEAF

HAND SANITIZER - 70% V/V ALCOHOL DENAT

ACTIVE INGREDIENT

ALCOHOL DENAT. 70% V/V

PURPOSE

ANTISEPTIC

USES

HAND SANITIZER TO HELP REDUCE BACTERIA ON THE SKIN

WARNINGS

Flammable. Keep away from fire or flame. For external use only. Do not ingest, if swallowed seek medical help. Avoid contact with eyes.

Keep out of reach of children.

Children under 6 years old to use under adult supervision. in case of irritation, discontinue use and consult your doctor.

DIRECTIONS

Apply the gel on the hands and rub gently for 20 seconds until the product evaporates. allow to dry without wiping. Not recommended for infants.

OTHER INFORMATION

Store below 106°F (41°C). May discolor certain fabrics or surfaces.

INACTIVE INGREDIENTS

Alcohol denat., Water/Aqua, Acrylates/C10-30 Alkyl Crosspolymer, Aminomethyl propanol, Fragrance/Parfum, Glycerin, Citral*, Linalool*, Butylene glycol, Alor barbadensis leaf extract. *Naturally found in essential oils